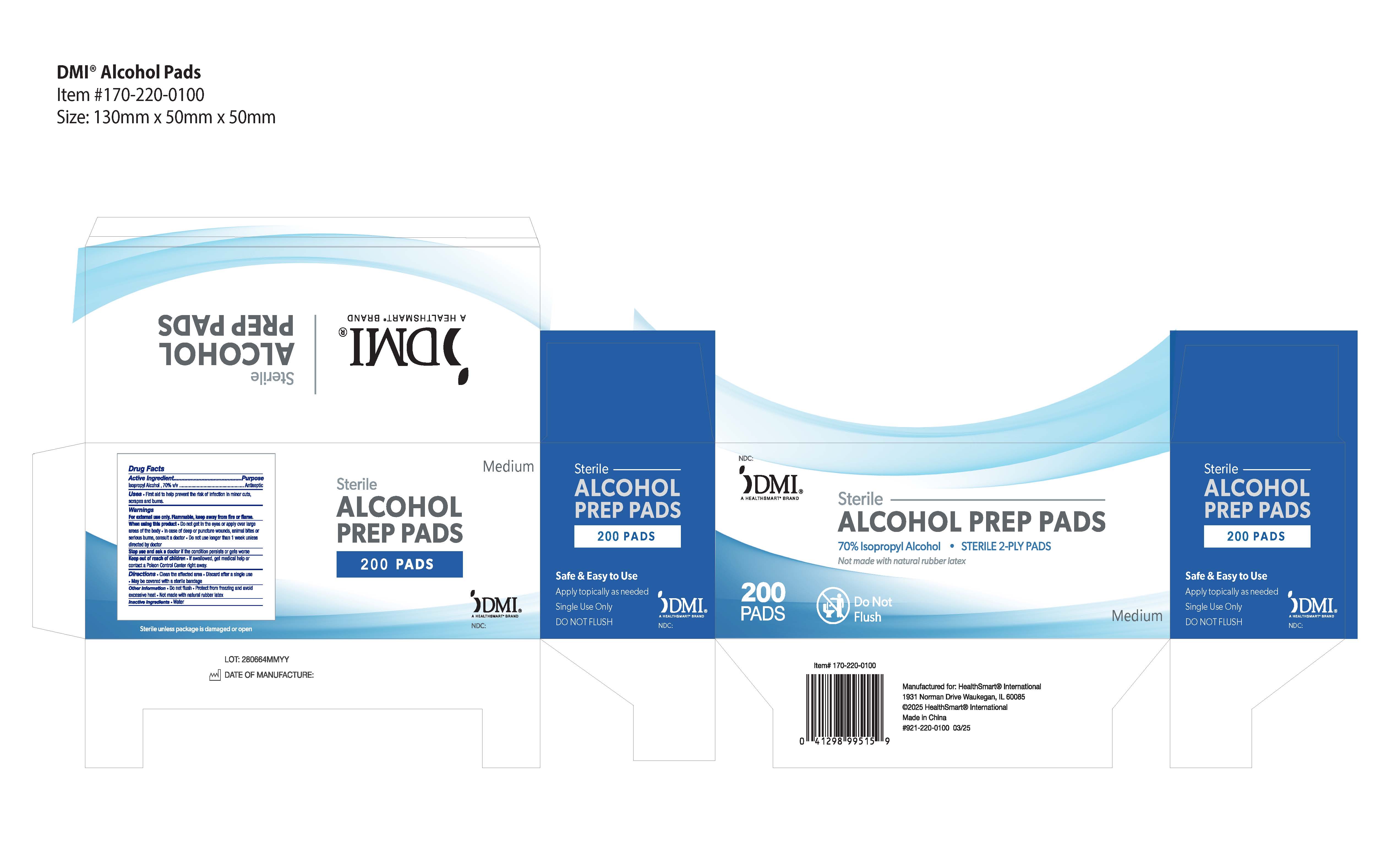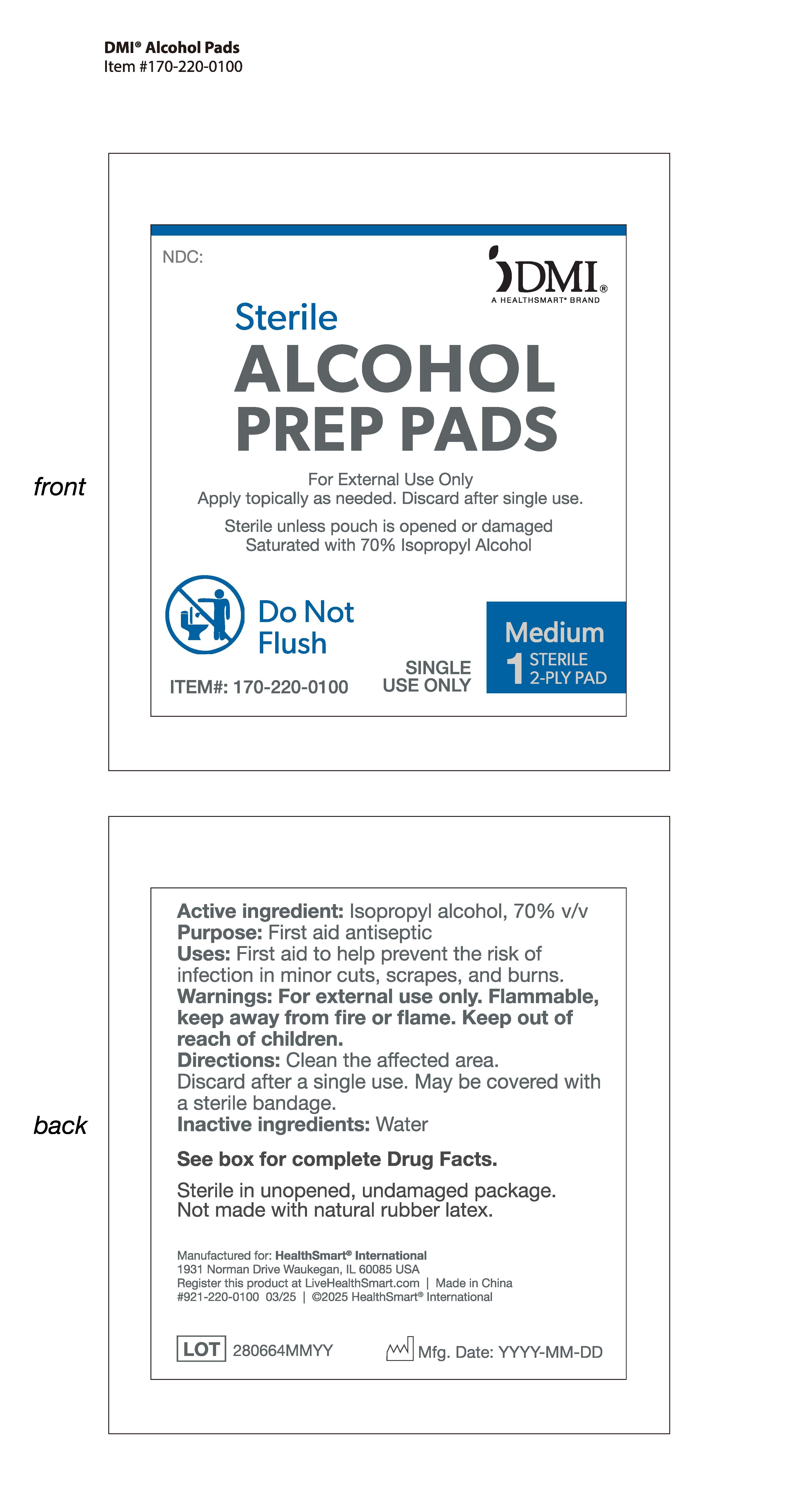 DRUG LABEL: ALCOHOL PREP PADS MEDIUM STERILE
NDC: 85734-001 | Form: CLOTH
Manufacturer: HUZHOU  JUNDA INDUSTRY CO., LTD.
Category: otc | Type: HUMAN OTC DRUG LABEL
Date: 20250527

ACTIVE INGREDIENTS: ISOPROPYL ALCOHOL 70 mL/100 mL
INACTIVE INGREDIENTS: WATER 30 mL/100 mL

ACTIVE INGREDIENT

Isopropyl Alcohol, 70% v/v

INACTIVE INGREDIENT

Purified Water

DESCRIPTION

First aid to help prevent the risk of infection in minor cuts, scrapes and burns.

WARNINGS

For external use only. Flammable, keep away from fire or flame.

When using this product • Do not get in the eyes or apply over large areas of the body • In case of deep or puncture wounds, animal bites or serious burns, consult a doctor • Do not use longer than 1 week unless directed by doctor
Stop use and ask a doctor if the condition persists or gets worse

Keep out of reach of children • If swallowed, get medical help or contact a Poison Control Center right away.

PURPOSE

Antiseptic

KEEP OUT OF REACH OF CHILDREN

• If swallowed, get medical help or contact a Poison Control Center right away.

INDICATIONS AND USAGE

Clean the affected area • Discard after a single use • May be covered with a sterile bandage

DOSAGE AND ADMINISTRATION

Apply topically as needed to cleanse intendend area.

OTHER SAFETY INFORMATION

•Do not flush • Protect from freezing and avoid excessive heat • Not made with natural rubber latex